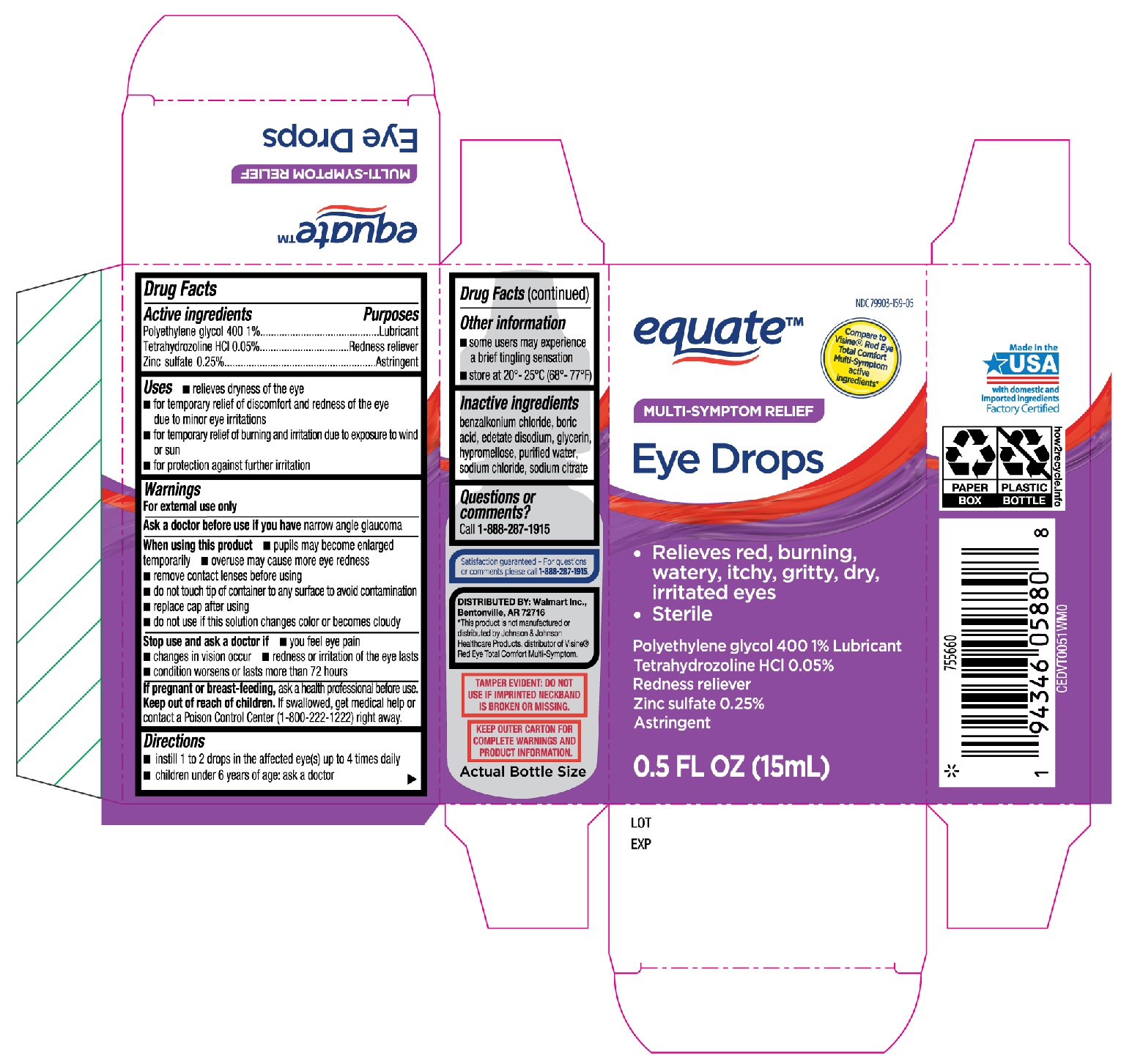 DRUG LABEL: Equate Multi-Symptom Relief Eye Drops
NDC: 79903-159 | Form: SOLUTION/ DROPS
Manufacturer: Walmart, Inc.
Category: otc | Type: HUMAN OTC DRUG LABEL
Date: 20251230

ACTIVE INGREDIENTS: ZINC SULFATE 0.25 g/100 mL; POLYETHYLENE GLYCOL 400 1 g/100 mL; TETRAHYDROZOLINE HYDROCHLORIDE 0.05 g/100 mL
INACTIVE INGREDIENTS: HYPROMELLOSE, UNSPECIFIED; WATER; BENZALKONIUM CHLORIDE; GLYCERIN; SODIUM CHLORIDE; BORIC ACID; EDETATE DISODIUM; SODIUM CITRATE

Equate Multi-Symptom Relief Eye Drops 15mL (PLD)

Active ingredients

Polyethylene glycol 400 1%

Tetrahydrozoline HCl 0.05%

Zinc Sulfate 0.25%

Purposes

Lubricant

Redness reliever

Astringent

Uses

- relieves dryness of the eye
- for temporary relief of discomfort and redness of the eye due to minor eye irritations
- for temporary relief of burning and irritation due to exposure to wind or sun
- for protection against further irritation

Warnings

For external use only

Ask a doctor before use if you have

narrow angle glaucoma

When using this product

- pupils may become enlarged temporarily
- overuse may cause more eye redness
- remove contact lenses before using
- do not touch tip of container to any surface to avoid contamination
- replace cap after using
- do not use if this solution changes color or becomes cloudy

Stop use and ask a doctor if

- you feel eye pain
- changes in vision occur
- redness or irritation of the eye lasts
- condition worsens or lasts more than 72 hours

If pregnant or breast-feeding,

ask a health professional before use.

Keep out of reach of chlidren.

If swallowed, get medical help or contact a Poison Control Center (1-800-222-1222) right away.

Directions

- instill 1 or 2 drops in the affected eye(s) up to 4 times daily
- children under 6 years of age: ask a doctor

Other information

- some users may experience a brief tingling sensation
- store at 20°-25°C (68°-77°F)

Inactive ingredints

benzalkonium chloride, boric acid, edetate disodium, glycerin, hypromellose, purified water, sodium chloride, sodium citrate

Questions or comments?

Call 1-888-287-1915